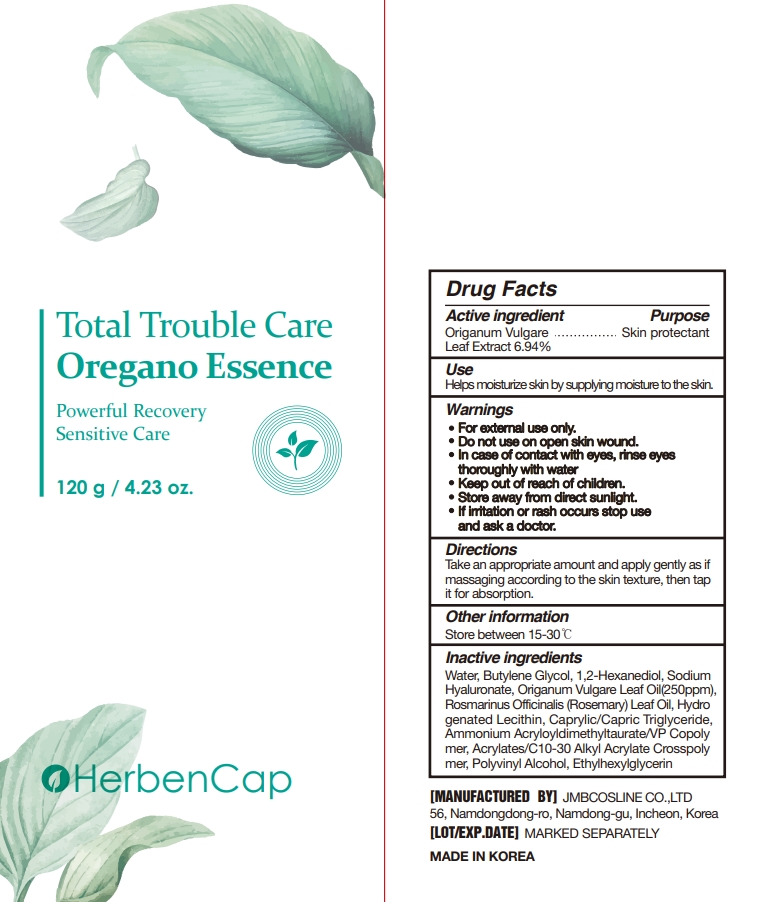 DRUG LABEL: Oregano Essence
NDC: 90028-201 | Form: LIQUID
Manufacturer: JMB COSLINE CO.,LTD
Category: otc | Type: HUMAN OTC DRUG LABEL
Date: 20201113

ACTIVE INGREDIENTS: OREGANO 6.94 g/100 g
INACTIVE INGREDIENTS: ETHYLHEXYLGLYCERIN; WATER; CARBOMER INTERPOLYMER TYPE A (55000 CPS); 1,2-HEXANEDIOL; MEDIUM-CHAIN TRIGLYCERIDES; AMMONIUM ACRYLOYLDIMETHYLTAURATE/VP COPOLYMER; POLYVINYL ALCOHOL, UNSPECIFIED; OREGANO LEAF OIL; HYALURONATE SODIUM; BUTYLENE GLYCOL; ROSEMARY OIL; HYDROGENATED SOYBEAN LECITHIN

90028-201

Active ingredient

Origanum Vulgare Leaf Extract 6.94%

Purpose

Skin protectant

Use

Helps moisturize skin by supplying moisture to the skin.

Warnings

- For external use only.
- Do not use on open skin wound.
- In case of contact with eyes, rinse eyes thoroughly with water
- Store away from direct sunlight.

Warnings

- Keep out of reach of children.

Warnings

If irritation or rash occurs stop use and ask a doctor.

Directions

Take an appropriate amount and apply gently as if massaging according to the skin texture, then tap it for absorption.

Other information

Store between 15-30℃

Inactive ingredients

Water, Butylene Glycol, 1,2-Hexanediol, Sodium Hyaluronate, Origanum Vulgare Leaf Oil(250ppm), Rosmarinus Officinalis (Rosemary) Leaf Oil, Hydro genated Lecithin, Caprylic/Capric Triglyceride, Ammonium Acryloyldimethyltaurate/VP Copoly mer, Acrylates/C10-30 Alkyl Acrylate Crosspoly mer, Polyvinyl Alcohol, Ethylhexylglycerin